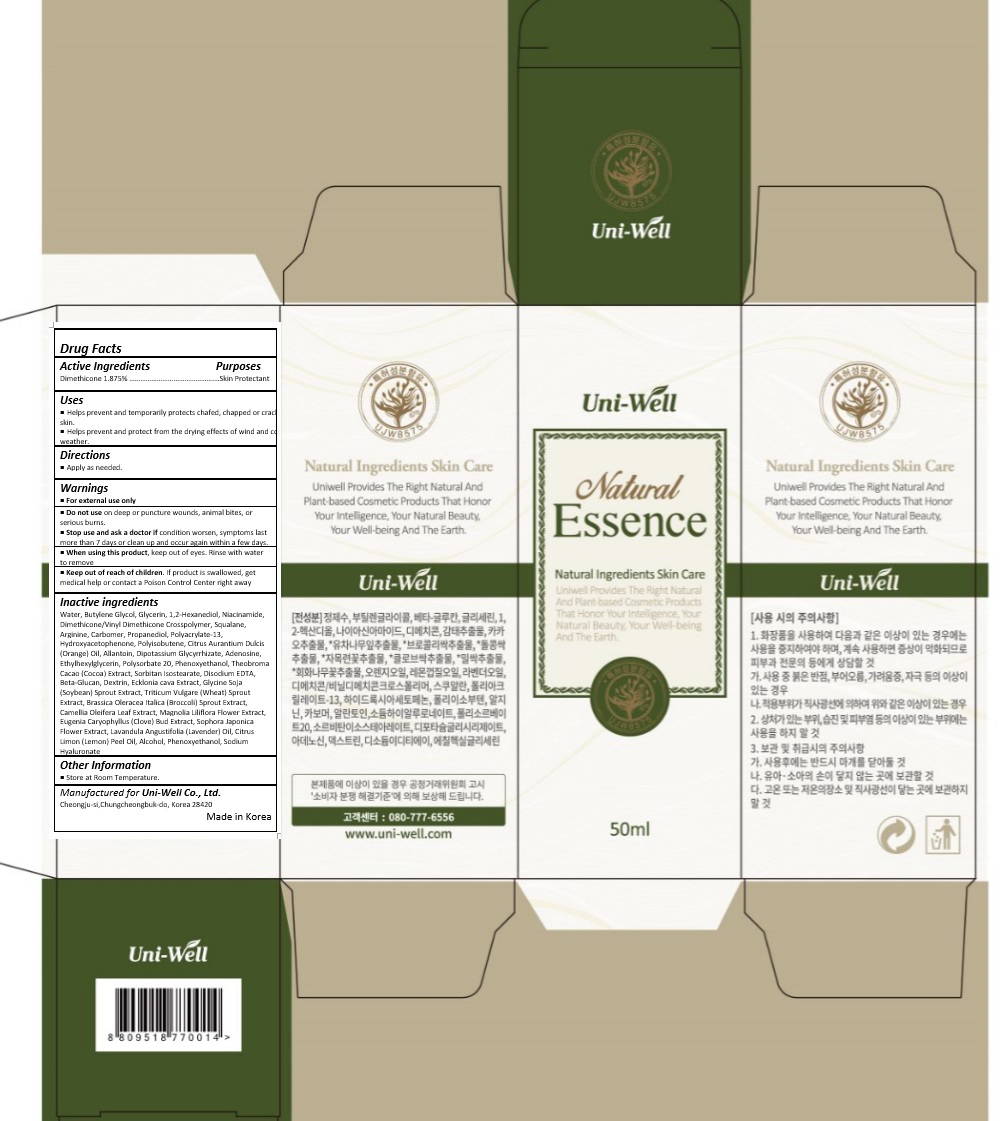 DRUG LABEL: UNIWELL NATURAL ESSENCE
NDC: 71502-002 | Form: EMULSION
Manufacturer: uniwell LTD
Category: otc | Type: HUMAN OTC DRUG LABEL
Date: 20170612

ACTIVE INGREDIENTS: DIMETHICONE 0.937 mg/50 mL
INACTIVE INGREDIENTS: WATER; Butylene Glycol; Glycerin; 1,2-Hexanediol; NIACINAMIDE; Squalane; Arginine; Propanediol; POLYACRYLAMIDE (1500 MW); 2-HYDROXYACETOPHENONE; POLYISOBUTYLENE (1000 MW); ORANGE OIL; Allantoin; GLYCYRRHIZINATE DIPOTASSIUM; Adenosine; Ethylhexylglycerin; Polysorbate 20; COCOA; SORBITAN ISOSTEARATE; EDETATE DISODIUM ANHYDROUS; ECKLONIA CAVA; SOYBEAN; WHEAT SPROUT; BROCCOLI SPROUT; CAMELLIA OLEIFERA LEAF; MAGNOLIA LILIIFLORA FLOWER; CLOVE; STYPHNOLOBIUM JAPONICUM FLOWER; LAVENDER OIL; LEMON OIL; ALCOHOL; Phenoxyethanol; HYALURONATE SODIUM

Drug Facts

ACTIVE INGREDIENT

DIMETHICONE 1.875%

PURPOSE

Skin Protectant

INDICATIONS AND USAGE

Helps prevent and temporarily protects chafed, chapped or cracked skin.
Helps prevent and protect from the drying effects of wind and cold weather.

DOSAGE AND ADMINISTRATION

Apply as needed.

WARNINGS

For external use only.
Do not use on deep or puncture wounds, animal bites, or serious burns.
Stop use and ask a doctor if condition worsen, symptoms last more than 7 days or clean up and occur again within a few days.

KEEP OUT OF REACH OF CHILDREN

Keep out of reach of the children. If product is swallowed, get medical help or contact a poison control center right away.

INACTIVE INGREDIENT

Water, Butylene Glycol, Glycerin, 1,2-Hexanediol, Niacinamide, Dimethicone/Vinyl Dimethicone Crosspolymer, Squalane, Arginine, Carbomer, Propanediol, Polyacrylate-13, Hydroxyacetophenone, Polyisobutene, Citrus Aurantium Dulcis (Orange) Oil, Allantoin, Dipotassium Glycyrrhizate, Adenosine, Ethylhexylglycerin, Polysorbate 20, Phenoxyethanol, Theobroma Cacao (Cocoa) Extract, Sorbitan Isostearate, Disodium EDTA, Beta-Glucan, Dextrin, Ecklonia cava Extract, Glycine Soja (Soybean) Sprout Extract, Triticum Vulgare (Wheat) Sprout Extract, Brassica Oleracea Italica (Broccoli) Sprout Extract, Camellia Oleifera Leaf Extract, Magnolia Liliflora Flower Extract, Eugenia Caryophyllus (Clove) Bud Extract, Sophora Japonica Flower Extract, Lavandula Angustifolia (Lavender) Oil, Citrus Limon (Lemon) Peel Oil, Alcohol, Phenoxyethanol, Sodium Hyaluronate